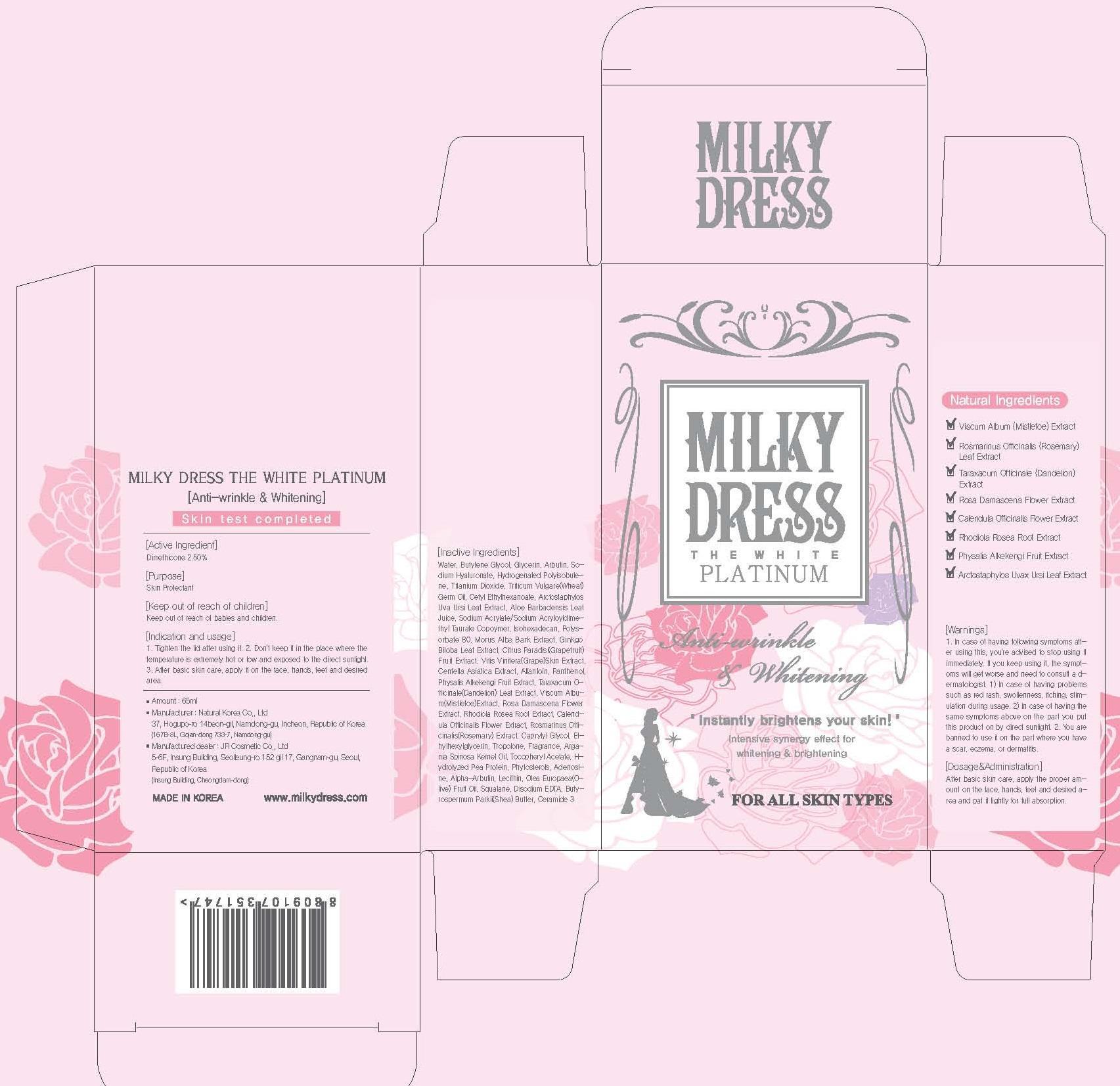 DRUG LABEL: Milky Dress The White Platinum
NDC: 69199-010 | Form: CREAM
Manufacturer: JR Cosmetic Co., Ltd
Category: otc | Type: HUMAN OTC DRUG LABEL
Date: 20140926

ACTIVE INGREDIENTS: Dimethicone 1.62 mg/65 mL
INACTIVE INGREDIENTS: Water; Butylene Glycol

ACTIVE INGREDIENT

Active Ingredient: Dimethicone 2.50%

INACTIVE INGREDIENT

Inactive Ingredients:
Water, Butylene Glycol, Glycerin, Arbutin, Sodium Hyaluronate, Hydrogenated Polyisobutene, Titanium Dioxide, Triticum Vulgare(Wheat) Germ Oil, Cetyl Ethylhexanoate, Arctostaphylos Uva Ursi Leaf Extract, Aloe Barbadensis Leaf Juice, Sodium Acrylate/Sodium Acryloyldimethyl Taurate Copoymer, Isohexadecan, Polysorbate 80, Morus Alba Bark Extract, Ginkgo Biloba Leaf Extract, Citrus Paradisi(Grapefruit)Fruit Extract, Vitis Vinifera(Grape)Skin Extract, Centella Asiatica Extract, Allantoin, Panthenol, Physalis Alkekengi Fruit Extract, Taraxacum Officinale(Dandelion) Leaf Extract, Viscum Album(Mistletoe)Extract, Rosa Damascena Flower Extract, Rhodiola Rosea Root Extract, Calendula Officinalis Flower Extract, Rosmarinus Officinalis(Rosemary) Extract,Caprylyl Glycol, Ethylhexylglycerin, Tropolone, Fragrance, Argania Spinosa Kernel Oil, Tocopheryl Acetate, Hydrolyzed Pea Protein, Phytosterols, Adenosine, Alpha-Arbutin, Lecithin, Olea Europaea(Olive) Fruit Oil,
Squalane, Disodium EDTA, Butyrospermum Parkii(Shea) Butter, Ceramide 3

PURPOSE

Purpose: Skin Protectant

WARNINGS

1. In case of having following symptoms after using this, you're advised to stop using it immediately.
If you keep using it, the symptoms will get worse and need to consult a dermatologist.
1) In case of having problems such as red rash, swollenness, itching, stimulation during usage.
2) In case of having the same symptoms above on the part you put this product on by direct sunlight.
2. You are banned to use it on the part where you have a scar, eczema, or dermatitis.

KEEP OUT OF REACH OF CHILDREN

Keep out of reach of babies and children.

INDICATIONS & USAGE

Indication and usage:
1. Tighten the lid after using it.
2. Don't keep it in the place where the temperature is extremely hot or low and exposed to the direct sunlight.
3. After basic skin care, apply it on the face, hands, feet and desired area.

DOSAGE & ADMINISTRATION

After basic skin care, apply the proper amount on the face, hands, feet and desired area and pat it lightly for full absorption.